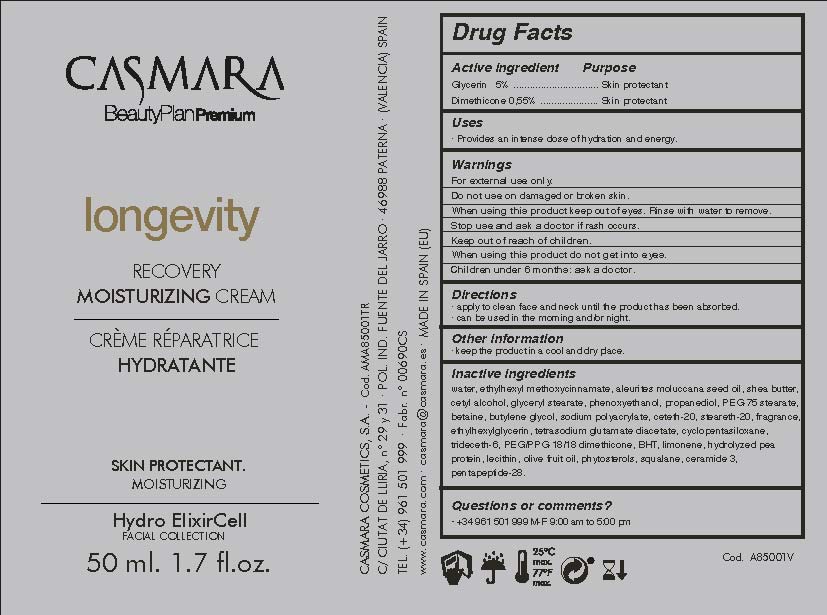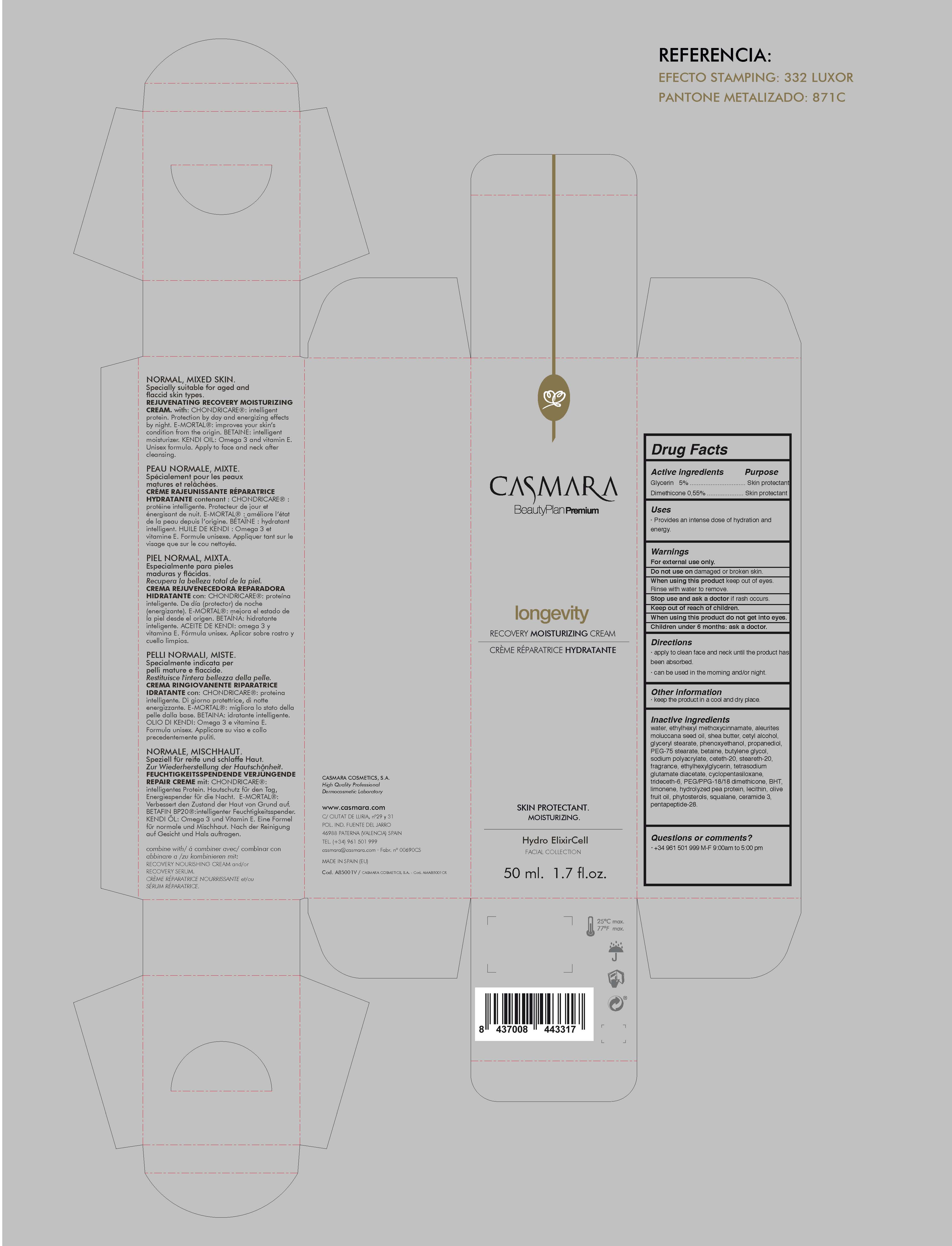 DRUG LABEL: Longevity Recovery Moisturizing
NDC: 20151-100 | Form: CREAM
Manufacturer: Casmara Cosmetics, SA
Category: otc | Type: HUMAN OTC DRUG LABEL
Date: 20170329

ACTIVE INGREDIENTS: GLYCERIN 5 mg/1 mL; DIMETHICONE 0.55 mg/1 mL
INACTIVE INGREDIENTS: CETYL ALCOHOL 1.125 mg/1 mL; ETHYLHEXYLGLYCERIN 0.1 mg/1 mL; WATER 80.853 mg/1 mL; PROPANEDIOL 0.75 mg/1 mL; PHENOXYETHANOL 0.9 mg/1 mL; OCTINOXATE 3 mg/1 mL; TETRASODIUM GLUTAMATE DIACETATE 0.094 mg/1 mL; ALEURITES MOLUCCANA SEED 2 mg/1 mL; TRIDECETH-6 0.075 mg/1 mL; PEA PROTEIN 0.01 mg/1 mL; LIMONENE, (+)- 0.014 mg/1 mL; OLIVE OIL 0.01 mg/1 mL; SQUALANE 0.01 mg/1 mL; SHEA BUTTER 2 mg/1 mL; CERAMIDE 3 0.01 mg/1 mL; BUTYLATED HYDROXYTOLUENE 0.023 mg/1 mL; HYDROGENATED SOYBEAN LECITHIN 0.01 mg/1 mL; GLYCERYL STEARATE SE 1.125 mg/1 mL; PEG-75 STEARATE 0.525 mg/1 mL; BETAINE 0.5 mg/1 mL; SODIUM POLYACRYLATE (2500000 MW) 0.25 mg/1 mL; CETETH-20 0.225 mg/1 mL; STEARETH-20 0.225 mg/1 mL; PEG/PPG-18/18 DIMETHICONE 0.03 mg/1 mL; CYCLOMETHICONE 5 0.075 mg/1 mL; BUTYLENE GLYCOL 0.3 mg/1 mL; PENTAPEPTIDE-31 0.00005 mg/1 mL; SOY STEROL 0.01 mg/1 mL

Longevity Recovery Moisturizing Cream

ACTIVE INGREDIENTS PURPOSE

Glycerin 5%.................... Skin Protectant

Dimethicone 0.55%........ Skin Protectant

Warnings

For external use only.

Do not use on damaged or broken skin.

When using this product keep our of the eyes. Rinse with water to remove.

Stop use and ask a doctor if rash occurs.

Keep out of reach of children.

Whhen using this product do not get into eyes.

Children under 6 months: as a doctor.

WARNINGS

Stop use and ask a doctor if rash occurs

Children under 6 months: ask a doctor

Warnings

Keep out of reach of children

Questions or comments?

+ 34 961 501 999 M-F 9:00 am to 5:00 pm

Other Information

. keep the product in a cool and dry place

Directions

. apply to clean face and neck until the product has been absorbed

. can be used in the morning and/or night

DOSAGE AND ADMINISTRATION

. apply to clean face and neck until the product has been absorbed

. can be used in the morning and/or night

Uses

. provides an intense dose of hydration and energy

Inactive Ingredients

Water, Ethylhexyl methoxycinnamate, Aleurites moluccana seed oil, Shea butter, Cetyl alcohol, Glyceryl stearate, Phenoxyethanol, Propanediol, PEG-75 stearate, Betaine, Butylene glycol, Sodium polyacrylate, Ceteth-20, Steareth-20, Fragrance, Ethylhexylglycerin, Tetrasodium glutamate diacetate, Cyclopentasiloxane, Trideceth-6, PEG/PPG- 18/18 dimethicone, BHT, Limonene, Hydrolyzed pea protein, Lecithin, Olive fruit oil, soy sterol, Squalane, Ceramide-3, Pentapeptide-31

Uses

. provides an intense dose of hydration and energy